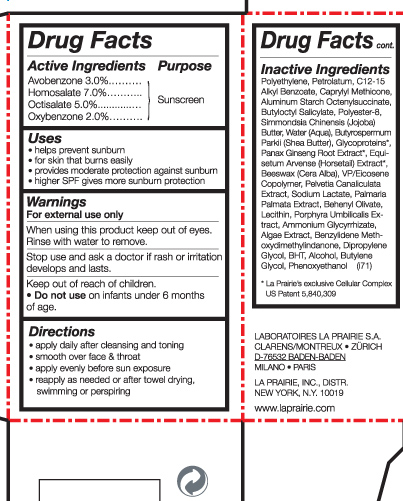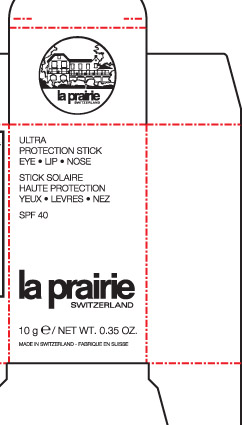 DRUG LABEL: Ultra Protection stick
NDC: 59614-738 | Form: STICK
Manufacturer: Juvena Produits De Beaute GMBH
Category: otc | Type: HUMAN OTC DRUG LABEL
Date: 20110214

ACTIVE INGREDIENTS: AVOBENZONE 3 g/100 g; HOMOSALATE 7 g/100 g; OCTISALATE 5 g/100 g; OXYBENZONE 2 g/100 g
INACTIVE INGREDIENTS: PETROLATUM; ALUMINUM STARCH OCTENYLSUCCINATE; BUTYLOCTYL SALICYLATE; GLYCYRRHIZIN, AMMONIATED; DIPROPYLENE GLYCOL; BUTYLATED HYDROXYTOLUENE; ALCOHOL; BUTYLENE GLYCOL

Ultra Protection stick SPF 40

Active ingredients

Avobenzone 3%

Homosalate 7%

Octisalate 5%

Oxybenzone 2%

Uses

helps prevent sunburn

for skin that burns easily

provides moderate protection against sunburn

higher spf gives more sunburn protection

Keep out of reach of children

Do not use on infants under 6 months of age

Stop use and ask a doctor if rash or irritation develops and lasts.

When using this product, keep out of eyes. Rinse with water to remove.

directions:

apply daily after cleansing and toning
smooth over face and throat
apply evenly before sun exposure
reapply as needed or after towel drying, swimming, or perspiring.

INACTIVE INGREDIENT

Polyethylene, Protrolatum, C12-15 Alkyl Benzoate, Caprylyl Methicone, Aluminum starch, Octenylsuccinate, Butyloctyl Salicylate, Polyester-8, Simmondsia Chinensis (jojoba) Butter, Water(Aqua), Butyrospermum Parkii (Shea Butter). Glycoproteins, Panax Singseng Root Extract, Equisetum Arvense (Horsetail) Extract, Beewax (cera Alba), VP/Eicosene Copolymer, Pelvetia Canaliculata Extract, Soduim Lactate, Palmaria Palmata Extract, Behenyl Olivate, Lecithin, Porphyra Umbilicalis Extract, Ammonium Glycyrrhizate, Algae Extract, Benzylidene Methoxydimethylindanone, Dipropylene Glycol, BHT, Alcohol, Butylene, Glycol, Phenoxyethanol.

PACKAGE LABEL

Ultra protection stick eye -lip-nose

10g/Net wt. 0.35 Oz.